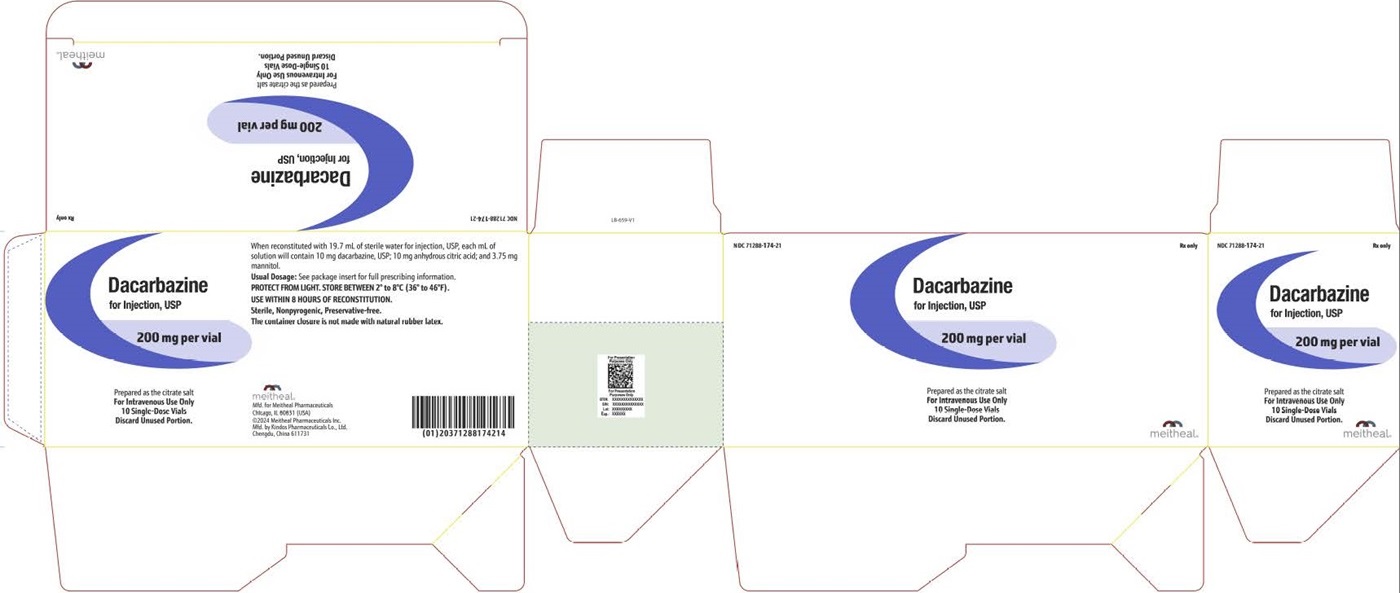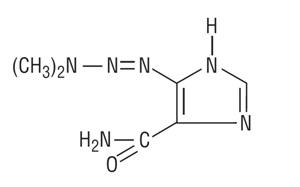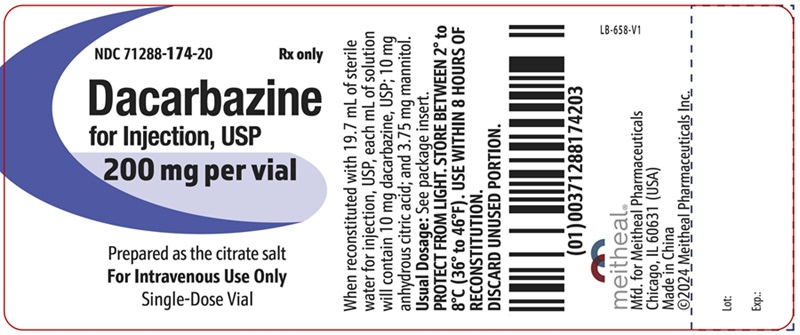 DRUG LABEL: Dacarbazine
NDC: 71288-174 | Form: INJECTION, POWDER, FOR SOLUTION
Manufacturer: Meitheal Pharmaceuticals Inc.
Category: prescription | Type: HUMAN PRESCRIPTION DRUG LABEL
Date: 20240322

ACTIVE INGREDIENTS: DACARBAZINE 200 mg/20 mL
INACTIVE INGREDIENTS: ANHYDROUS CITRIC ACID; MANNITOL

Dacarbazine for Injection, USP
For Intravenous Use Only
meitheal®
Rx only

WARNING

It is recommended that dacarbazine for injection be administered under the supervision of a qualified physician experienced in the use of cancer chemotherapeutic agents.

1. Hemopoietic depression is the most common toxicity with dacarbazine for injection. (See WARNINGS.)
2. Hepatic necrosis has been reported. (See WARNINGS.)
3. Studies have demonstrated this agent to have a carcinogenic and teratogenic effect when used in animals.
4. In treatment of each patient, the physician must weigh carefully the possibility of achieving therapeutic benefit against the risk of toxicity.

DESCRIPTION

Dacarbazine for Injection, USP is a white to an ivory colored solid which is light sensitive. Each 20 mL vial contains 200 mg of dacarbazine, USP (active ingredient). Each vial also contains anhydrous citric acid and mannitol. Dacarbazine for Injection, USP is reconstituted and administered intravenously (pH 3.0 to 4.0). Dacarbazine for Injection, USP is an anticancer agent. Chemically, Dacarbazine for Injection, USP is 5-(3,3-Dimethyl-1-triazeno) imidazole-4-carboxamide (dacarbazine) with the following structural formula:

C6H10N6O

M.W. 182.19

CLINICAL PHARMACOLOGY

After intravenous administration of dacarbazine for injection, the volume of distribution exceeds total body water content suggesting localization in some body tissue, probably the liver. Its disappearance from the plasma is biphasic with initial half-life of 19 minutes and a terminal half-life of 5 hours.^1 In a patient with renal and hepatic dysfunctions, the half-lives were lengthened to 55 minutes and 7.2 hours.^1 The average cumulative excretion of unchanged dacarbazine in the urine is 40% of the injected dose in 6 hours.^1

Dacarbazine is subject to renal tubular secretion rather than glomerular filtration. At therapeutic concentrations dacarbazine is not appreciably bound to human plasma protein.

In man, dacarbazine is extensively degraded. Besides unchanged dacarbazine, 5-aminoimidazole-4 carboxamide (AIC) is a major metabolite of dacarbazine excreted in the urine. AIC is not derived endogenously but from the injected dacarbazine, because the administration of radioactive dacarbazine labeled with ^14C in the imidazole portion of the molecule (dacarbazine-2-^14C) gives rise to AIC-2-^14C.^1

Although the exact mechanism of action of dacarbazine for injection is not known, three hypotheses have been offered:

1. Inhibition of DNA synthesis by acting as a purine analog
2. Action as an alkylating agent
3. Interaction with SH groups

INDICATIONS AND USAGE

Dacarbazine for Injection is indicated in the treatment of metastatic malignant melanoma. In addition, Dacarbazine for Injection is also indicated for Hodgkin's disease as a secondary-line therapy when used in combination with other effective agents.

CONTRAINDICATIONS

Dacarbazine for injection is contraindicated in patients who have demonstrated a hypersensitivity to it in the past.

WARNINGS

Hemopoietic depression is the most common toxicity with dacarbazine for injection and involves primarily the leukocytes and platelets, although anemia may sometimes occur. Leukopenia and thrombocytopenia may be severe enough to cause death. The possible bone marrow depression requires careful monitoring of white blood cells, red blood cells, and platelet levels. Hemopoietic toxicity may warrant temporary suspension or cessation of therapy with dacarbazine for injection.

Hepatic toxicity accompanied by hepatic vein thrombosis and hepatocellular necrosis resulting in death, has been reported. The incidence of such reactions has been low; approximately 0.01% of patients treated. This toxicity has been observed mostly when dacarbazine for injection has been administered concomitantly with other anti-neoplastic drugs; however, it has also been reported in some patients treated with dacarbazine for injection alone.

Anaphylaxis can occur following the administration of dacarbazine for injection.

PRECAUTIONS

Hospitalization is not always necessary but adequate laboratory study capability must be available. Extravasation of the drug subcutaneously during intravenous administration may result in tissue damage and severe pain. Local pain, burning sensation, and irritation at the site of injection may be relieved by locally applied hot packs.

Carcinogenicity of dacarbazine was studied in rats and mice. Proliferative endocardial lesions, including fibrosarcomas and sarcomas were induced by dacarbazine in rats. In mice, administration of dacarbazine resulted in the induction of angiosarcomas of the spleen.

Pregnancy

Teratogenic Effects, Pregnancy Category C

Dacarbazine for injection has been shown to be teratogenic in rats when given in doses 20 times the human daily dose on day 12 of gestation. Dacarbazine when administered in 10 times the human daily dose to male rats (twice weekly for 9 weeks) did not affect the male libido, although female rats mated to male rats had higher incidence of resorptions than controls. In rabbits, dacarbazine daily dose 7 times the human daily dose given on days 6 to 15 of gestation resulted in fetal skeletal anomalies. There are no adequate and well controlled studies in pregnant women. Dacarbazine for injection should be used during pregnancy only if the potential benefit justifies the potential risk to the fetus.

It is not known whether this drug is excreted in human milk. Because many drugs are excreted in human milk and because of the potential for tumorigenicity shown for dacarbazine for injection in animal studies, a decision should be made whether to discontinue nursing or to discontinue the drug, taking into account the importance of the drug to the mother.

ADVERSE REACTIONS

Symptoms of anorexia, nausea, and vomiting are the most frequently noted of all toxic reactions. Over 90% of patients are affected with the initial few doses. The vomiting lasts 1 to 12 hours and is incompletely and unpredictably palliated with phenobarbital and/or prochlorperazine. Rarely, intractable nausea and vomiting have necessitated discontinuance of therapy with dacarbazine for injection. Rarely, dacarbazine for injection has caused diarrhea. Some helpful suggestions include restricting the patient's oral intake of food for 4 to 6 hours prior to treatment. The rapid toleration of these symptoms suggests that a central nervous system mechanism may be involved, and usually these symptoms subside after the first 1 or 2 days.

There are a number of minor toxicities that are infrequently noted. Patients have experienced an influenza-like syndrome of fever to 39°C, myalgias and malaise. These symptoms occur usually after large single doses, may last for several days, and they may occur with successive treatments.

Alopecia has been noted as has facial flushing and facial paresthesia. There have been few reports of significant liver or renal function test abnormalities in man. However, these abnormalities have been observed more frequently in animal studies.

Erythematous and urticarial rashes have been observed infrequently after administration of dacarbazine for injection. Rarely, photosensitivity reactions may occur.

To report SUSPECTED ADVERSE REACTIONS, contact Meitheal Pharmaceuticals, Inc. at 1-844-824-8426 or FDA at 1-800-FDA-1088 or www.fda.gov/medwatch.

OVERDOSAGE

Give supportive treatment and monitor blood cell counts.

DOSAGE AND ADMINISTRATION

Malignant Melanoma

The recommended dosage is 2 to 4.5 mg/kg/day for 10 days. Treatment may be repeated at 4 week intervals.^2

An alternate recommended dosage is 250 mg/square meter body surface/day IV for 5 days. Treatment may be repeated every 3 weeks.^(3, 4)

Hodgkin's Disease

The recommended dosage of dacarbazine for injection in the treatment of Hodgkin's Disease is 150 mg/square meter body surface/day for 5 days, in combination with other effective drugs. Treatment may be repeated every 4 weeks.^5 An alternative recommended dosage is 375 mg/square meter body surface on day 1, in combination with other effective drugs, to be repeated every 15 days.^6

Dacarbazine for injection 200 mg/vial is reconstituted with 19.7 mL of sterile water for injection, USP. Dacarbazine for injection 500 mg/vial is reconstituted with 49.25 mL of sterile water for injection, USP. The resulting solution contains 10 mg/mL of dacarbazine having a pH of 3.0 to 4.0. The calculated dose of the resulting solution is drawn into a syringe and administered only intravenously.

The reconstituted solution may be further diluted with 5% dextrose injection or sodium chloride injection and administered as an intravenous infusion.

After reconstitution and prior to use, the solution in the vial may be stored at 4°C for up to 72 hours or at normal room conditions (temperature and light) for up to 8 hours. If the reconstituted solution is further diluted in 5% dextrose injection or sodium chloride injection, the resulting solution may be stored at 4°C for up to 24 hours or at normal room conditions for up to 8 hours.

Procedures for proper handling and disposal of anticancer drugs should be considered. Several guidelines on this subject have been published.^7–12 There is no general agreement that all of the procedures recommended in the guidelines are necessary or appropriate.

HOW SUPPLIED

Sterile Dacarbazine for Injection, USP is available as follows:

NDC | Dacarbazine for Injection, USP | Package Factor
71288-174-21 | 200 mg Single-Dose Vial | 10 vials per carton

STORAGE AND HANDLING

Store in a refrigerator 2° to 8°C (36° to 46°F). Use within 8 hours of reconstitution. Protect from light.

DISCARD UNUSED PORTION.
Sterile, Nonpyrogenic, Preservative-free.
The container closure is not made with natural rubber latex.

REFERENCES

1. Loo, T.J., et al.: Mechanism of action and pharmacology studies with DTIC (NSC-45388). Cancer Treatment Reports 60: 149–152, 1976.
2. Nathanson, L., et al.: Characteristics of prognosis and response to an imidazole carboxamide in malignant melanoma. Clinical Pharmacology and Therapeutics 12: 955–962, 1971.
3. Costanza, M.E., et al.: Therapy of malignant melanoma with an imidazole carboxamide and bischloroethyl nitrosourea. Cancer 30: 1457–1461, 1972.
4. Luce, J.K., et al.: Clinical trials with the antitumor agent 5-(3, 3-dimethyl-1-triazeno) imidazole-4-carboxamide (NSC-45388). Cancer Chemotherapy Reports 54: 119–124, 1970.
5. Bonadonna, G., et al.: Combined Chemotherapy (MOPP or ABVD)—radiotherapy approach in advanced Hodgkin's disease. Cancer Treatment Reports 61: 769–777, 1977.
6. Santoro, A., and Bonadonna, G.: Prolonged disease-free survival in MOPP-resistant Hodgkin's disease after treatment with adriamycin, bleomycin, vinblastine and dacarbazine (ABVD).
  Cancer Chemotherapy Pharmacol. 2: 101–105, 1979.
7. Recommendations for the Safe Handling of Parenteral Antineoplastic Drugs, NIH Publication No. 83-2621. For sale by the Superintendent of Documents, U.S. Government Printing Office, Washington, DC 20402.
8. AMA Council Report, Guidelines for Handling Parenteral Antineoplastics, JAMA, 1985; 253 (11):1590–1592.
9. National Study Commission on Cytotoxic Exposure—Recommendations for Handling Cytotoxic Agents. Available from Louis P. Jeffrey, ScD., Chairman, National Study Commission on Cytotoxic Exposure, Massachusetts College of Pharmacy and Allied Health Sciences, 179 Longwood Avenue, Boston, Massachusetts 02115.
10. Clinical Oncological Society of Australia, Guidelines and Recommendations for Safe Handling of Antineoplastic Agents. Med. J. Australia, 1983; 1:426–428.
11. Jones, RB, et al.: Safe Handling of Chemotherapeutic Agents: A Report from the Mount Sinai Medical Center. CA—A Cancer Journal for Clinicians, 1983; (Sept/Oct) 258–263.
12. American Society of Hospital Pharmacists Technical Assistance Bulletin on Handling Cytotoxic and Hazardous Drugs. Am. J. Hosp. Pharm, 1990; 47: 1033–1049.
13. OSHA Work-Practice Guidelines for Personnel Dealing with Cytotoxic (Antineoplastic) Drugs. Am. J. Hosp. Pharm, 1986; 43:1193–1204.

meitheal®

Mfd. for Meitheal Pharmaceuticals
Chicago, IL 60631 (USA)
©2024 Meitheal Pharmaceuticals Inc.

Mfd. by Kindos Pharmaceuticals Co., Ltd.
Chengdu, China 611731

February 2024

LB-660-V1

PACKAGE LABEL PRINCIPAL DISPLAY PANEL Dacarbazine for Injection, USP Vial Label

NDC 71288-174-20

Rx only

Dacarbazine for Injection, USP

200 mg per vial

Prepared as the citrate salt

For Intravenous Use Only

Single-Dose Vial

PACKAGE LABEL PRINCIPAL DISPLAY PANEL Dacarbazine for Injection, USP Carton

NDC 71288-174-21

Rx only

Dacarbazine for Injection, USP

200 mg per vial

Prepared as the citrate salt

For Intravenous Use Only

10 Single-Dose Vials

Discard Unused Portion.